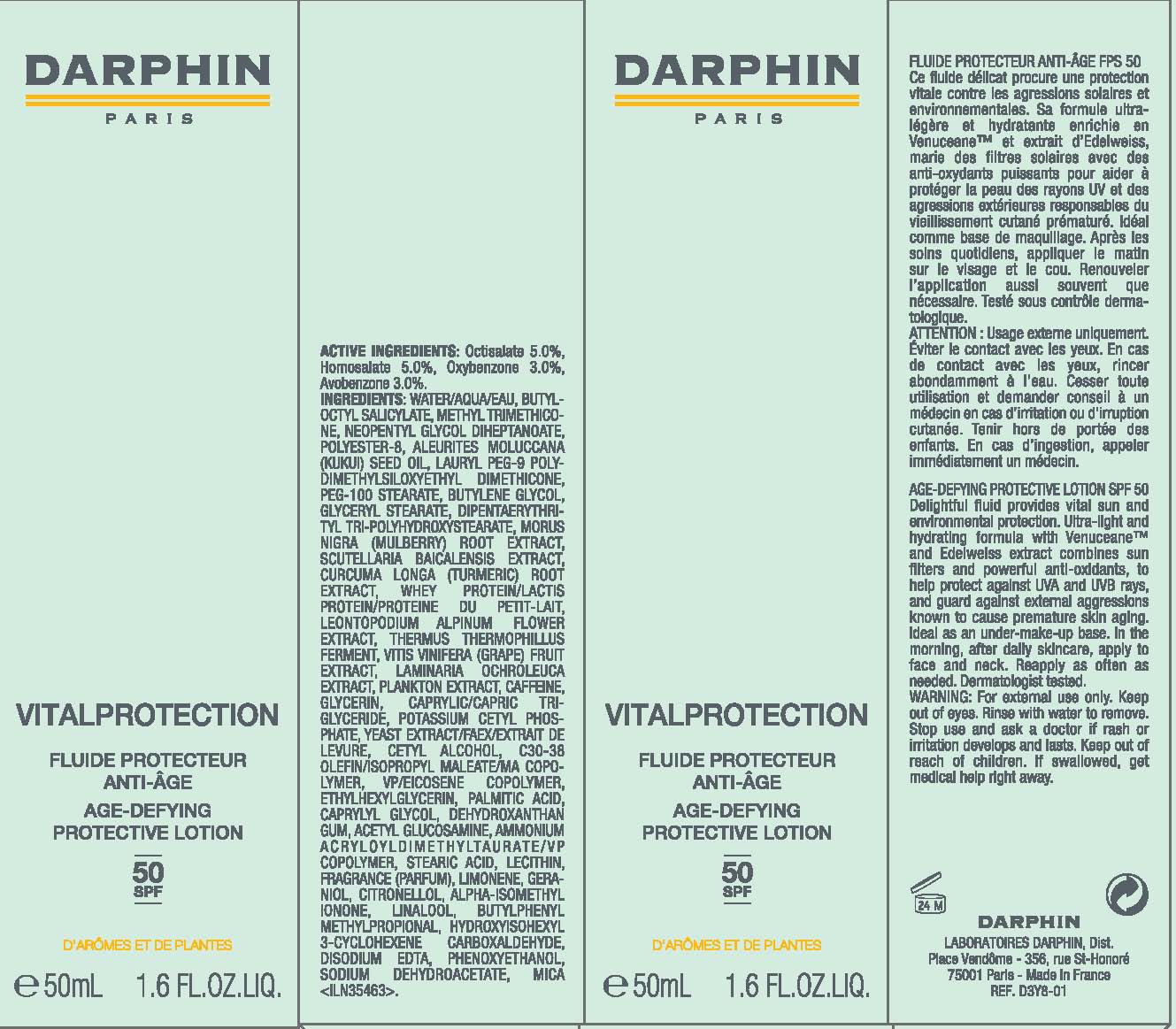 DRUG LABEL: VIALPROTECTION
NDC: 16555-006 | Form: LOTION
Manufacturer: DARPHIN DIST.
Category: otc | Type: HUMAN OTC DRUG LABEL
Date: 20100819

ACTIVE INGREDIENTS: HOMOSALATE 5.0 mL/100 mL; OCTISALATE 5.0 mL/100 mL; AVOBENZONE 3.0 mL/100 mL; OXYBENZONE 3.0 mL/100 mL
INACTIVE INGREDIENTS: WATER; METHYL TRIMETHICONE; NEOPENTYL GLYCOL DIHEPTANOATE; BUTYLOCTYL SALICYLATE; KUKUI NUT OIL; PEG-100 STEARATE; BUTYLENE GLYCOL; GLYCERYL MONOSTEARATE; MORUS AUSTRALIS ROOT; SCUTELLARIA BAICALENSIS ROOT; TURMERIC; WHEY; LEONTOPODIUM ALPINUM FLOWER; WINE GRAPE; CAFFEINE; GLYCERIN; MEDIUM-CHAIN TRIGLYCERIDES; POTASSIUM CETYL PHOSPHATE; YEAST; CETYL ALCOHOL; ETHYLHEXYLGLYCERIN; PALMITIC ACID; CAPRYLYL GLYCOL; N-ACETYLGLUCOSAMINE; STEARIC ACID; LECITHIN, SOYBEAN; EDETATE DISODIUM; PHENOXYETHANOL; SODIUM DEHYDROACETATE; MICA

ACTIVE INGREDIENT

ACTIVE INGREDIENTS: HOMOSALATE 5.00% [] OCTISALATE 5.00% [] AVOBENZONE 3.00% [] OXYBENZONE 3.00%

INACTIVE INGREDIENT

INGREDIENTS: WATER\AQUA\EAU [] BUTYLOCTYL SALICYLATE [] METHYL TRIMETHICONE [] NEOPENTYL GLYCOL DIHEPTANOATE [] POLYESTER-8 [] ALEURITES MOLUCCANA (KUKUI) SEED OIL [] LAURYL PEG-9 POLYDIMETHYLSILOXYETHYL DIMETHICONE [] PEG-100 STEARATE [] BUTYLENE GLYCOL [] GLYCERYL STEARATE [] DIPENTAERYTHRITYL TRI-POLYHYDROXYSTEARATE [] MORUS NIGRA (MULBERRY) ROOT EXTRACT [] SCUTELLARIA BAICALENSIS EXTRACT [] CURCUMA LONGA (TURMERIC) ROOT EXTRACT [] WHEY PROTEIN\LACTIS PROTEIN\PROTEINE DU PETIT-LAIT [] LEONTOPODIUM ALPINUM FLOWER EXTRACT [] THERMUS THERMOPHILLUS FERMENT [] VITIS VINIFERA (GRAPE) FRUIT EXTRACT [] LAMINARIA OCHROLEUCA EXTRACT [] PLANKTON EXTRACT [] CAFFEINE [] GLYCERIN [] CAPRYLIC/CAPRIC TRIGLYCERIDE [] POTASSIUM CETYL PHOSPHATE [] YEAST EXTRACT\FAEX\EXTRAIT DE LEVURE [] CETYL ALCOHOL [] C30-38 OLEFIN/ISOPROPYL MALEATE/MA COPOLYMER [] VP/EICOSENE COPOLYMER [] ETHYLHEXYLGLYCERIN [] PALMITIC ACID [] CAPRYLYL GLYCOL [] DEHYDROXANTHAN GUM [] ACETYL GLUCOSAMINE [] AMMONIUM ACRYLOYLDIMETHYLTAURATE/VP COPOLYMER [] STEARIC ACID [] LECITHIN [] FRAGRANCE (PARFUM) [] LIMONENE [] GERANIOL [] CITRONELLOL [] ALPHA-ISOMETHYL IONONE [] LINALOOL [] BUTYLPHENYL METHYLPROPIONAL [] HYDROXYISOHEXYL 3-CYCLOHEXENE CARBOXALDEHYDE [] DISODIUM EDTA [] PHENOXYETHANOL [] SODIUM DEHYDROACETATE [] MICA

WARNINGS

WARNING: FOR EXTERNAL USE ONLY. KEEP OUT OF EYES. RINSE WITH WATER TO REMOVE.STOP USE AND ASK A DOCTOR STOP USE IF IRRITATION OR IRRITATION DEVELOPS AND LASTS.

KEEP OUT OF REACH OF CHILDREN. IF SWALLOWED, GET MEDICAL HELP RIGHT AWAY

PACKAGE LABEL

PRINCIPAL DISPLAY PANEL

DARPHIN

VITALPROTECTION

AGE DEFYING

PROTECTIVE LOTION

SPF 50

1.6 FL OZ. LIQ/50 ML

DARPHIN DISTR.

PARIS, FRANCE